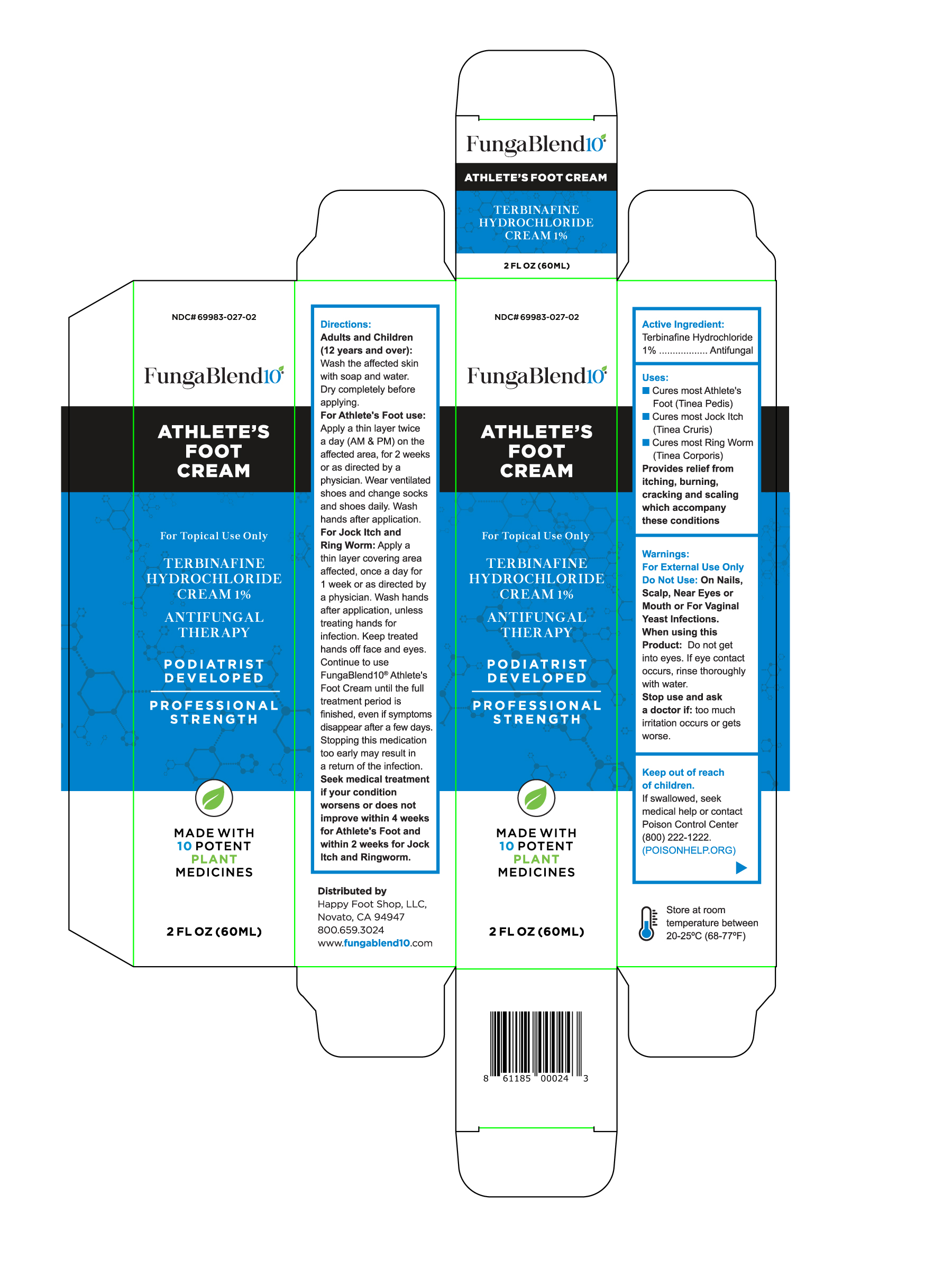 DRUG LABEL: Terbinafine Hydrochloride
NDC: 69983-027 | Form: CREAM
Manufacturer: Happy Foot Shop LLC
Category: otc | Type: HUMAN OTC DRUG LABEL
Date: 20241030

ACTIVE INGREDIENTS: TERBINAFINE HYDROCHLORIDE 1 g/100 g
INACTIVE INGREDIENTS: CITRUS LIMON (LEMON) LEAF OIL; PHENOXYPROPANEDIOL; SODIUM HYDROXIDE; PEG-9 DIGLYCIDYL ETHER/SODIUM HYALURONATE CROSSPOLYMER; ISOPROPYL MYRISTATE; STEARIC ACID D7; ALOE BARBADENSIS LEAF JUICE POWDER; CALCIUM DISODIUM EDTA; POLYMETHYLSILSESQUIOXANE; ALLANTOIN; GLYCERIN 1,3-DIMETHYL ETHER; LAVANDULA ANGUSTIFOLIA (LAVENDER) OIL; PROPYLENE GLYCOL; GLYCERYL STEARATE/PEG-75 STEARATE; DIMETHICONE CROSSPOLYMER; ROSMARINUS OFFICINALIS (ROSEMARY) LEAF OIL; THYMUS VULGARIS LEAF; WATER; XANTHAN GUM; MENTHOXYPROPANEDIOL; CETYL ALCOHOL; SODIUM ACRYLATE/SODIUM ACRYLOYLDIMETHYLTAURATE COPOLYMER (4000000 MW); MELALEUCA ALTERNIFOLIA (TEA TREE) LEAF

KEEP OUT OF REACH OF CHILDREN

For External Use Only

Do Not Use : On Nails, Scalp, Near Eyes or Mouth or For Vaginal Yeast Infections.

When using ths Product : Do not get into eyes. If eye contact occurs, rinse throughly with water.

Stop use and ask a doctor if : too much irritation occurs or gets worse.

Keep out of reach of children.

If swallowed , seek medical help or contact Poison Control Center (800) 222-1222

(POISONHELP.ORG)

Terbinafine Hydrochloride 1% ...................Antifungal

Active Ingredient :

Terbinafine Hydrochloride 1%

Antifungal

Indications & Usage

Uses :

- Cures most Athlete;s Foot (Tinea Pedis)
- Cures most Jock Itch (Tinea Pedis)
- Cures most Ring Worm (Tinea Corporis)

Provides relief from itching, burning, cracking and scalingwhich accompany these conditions.

Storage and Handling

Store at room temperature between 20-25°C (68-77°F)

Directions

Adults and Children (12 years and over) : Wash the affected skin with soap and water. Dry completely before applying.

For Athlete's Foot use : Apply a thin layer twice a day (AM & PM) on the affected area, for 2 weeks or as directed by a physician. Wear ventilated shoes and change socks and shoes daily. Wash hands after application.

For Jock Itch and Ring Worm : Apply a thin layer covering area affected, once a day for 1 week or as directed by a physician. Wash hands after application, unless treating hands for infection. Keep treated hands off face and eyes.

Continue to use FungaBlend10® Athlete's Foot Cream until the full treatment period is finished, even if symptoms disappear after a few days. Stopping this medication too early may result in a return of the infection.

Seek Medical Treatment if your condition worsens or does not improve within 4 weeks for Athlete's Foot and within 2 weeks for Jock Itch and Ringworm.

Questions about Product and Distribution

Distributed by :

Happy Foot Shop, LLC

Novato, CA 94947

800-659-3024

www.fungablend10.com

Inactive Ingredients

Distilled Water

Isopropyl Myristate

Aloe Barbadensis Leaf Juice Powder

Disodium EDTA

Glycerin

Allatoin

Xanthan Gum

Stearic Acid

Cetyl Alcohol

Glyceryl Stearate

Sodium Acrylate/Sodium Acryloydimethyl

Polymethylsilsesquioxane

Dimethicone

Sodium Hyaluronate Crosspolymer

Propylene Glycol

Citris Medica Limonum(Lemon) Oil

Lavandula Officinalis (Lavender) Oil

Melaleuca Altenafolia (Tea Tree) Oil

Rosmarinus Officinalis (Rosemary) Leaf Oil

Thymus Vulgarus (Thyme) Leaf Oil

Phenoxyethanol , Ethylhexlglycerin

Menthoxypropanediol

Sodium Hydroxide

Purpose

Antifungal

Warnings

FOR EXTERNAL USE ONLY

DO NOT USE ON : On Nails, Scalp, Near Eyes or Mouth or For Vaginal Yeast Infections.

When using this product: Do not get into eyes. If eye contact occurs, rinse throughly with water .

Stop use and ask a doctor if : too much irritation occurs or gets worse.

Keep Out of reach of Children. If swallowed, seek medical help or contact Poison Control Center (800) 222-1222

(POISONHELP.ORG)

FungaBlend 10® Athlete's Foot Cream

FungaBlend 10®

ATHLETE'S FOOT CREAM

For Topical Use Only

TERBINAFINE HYDROCHLORIDE CREAM 1%

ANTIFUNGAL THERAPY

PODIATRIST DEVELOPED

PROFESSIONAL STRENGTH

Made with 10 Potent Plant Medicines

2 FL OZ (60ML)